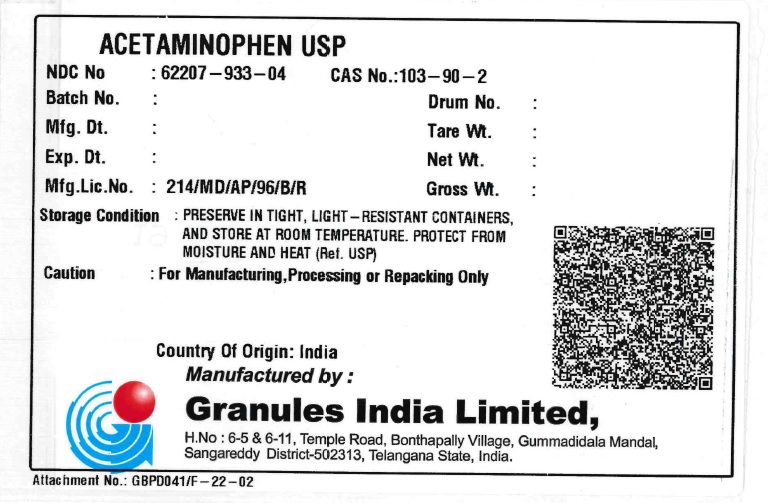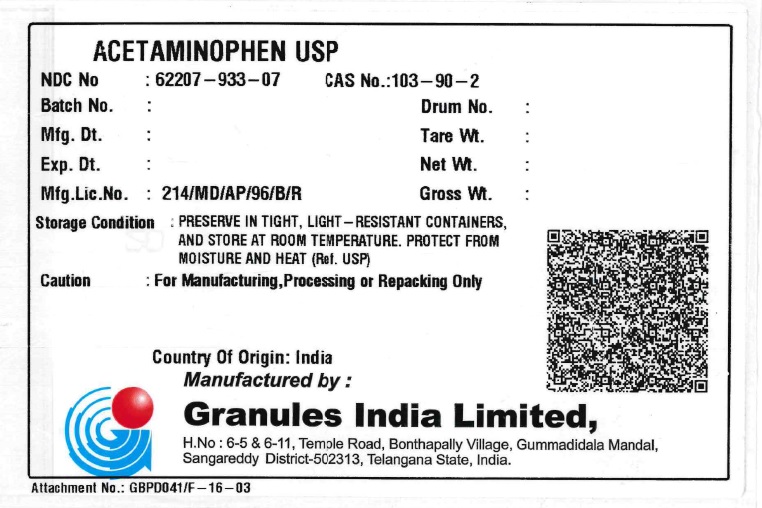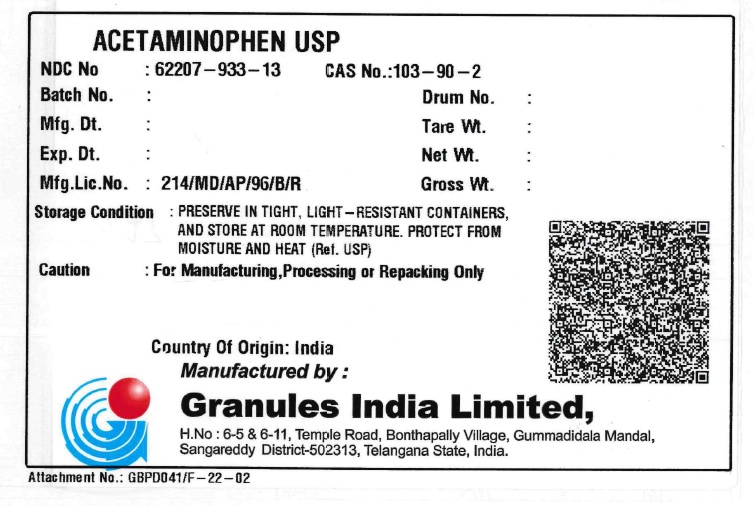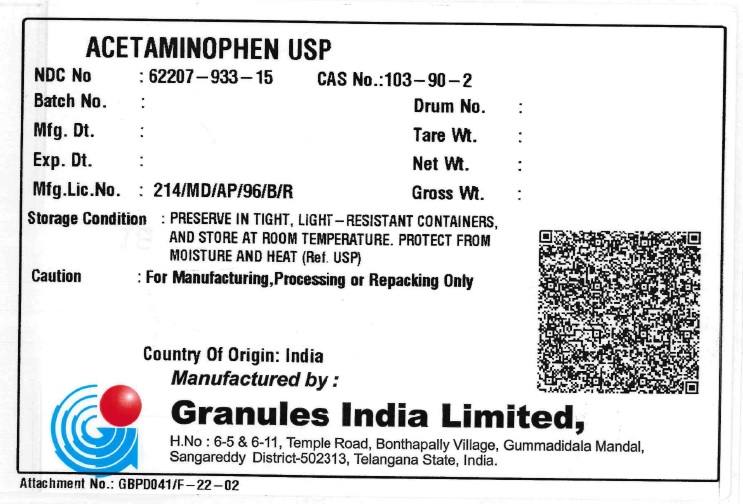 DRUG LABEL: Acetaminophen
NDC: 62207-933 | Form: POWDER
Manufacturer: Granules India Limited
Category: other | Type: BULK INGREDIENT
Date: 20251031

ACTIVE INGREDIENTS: ACETAMINOPHEN 1 kg/1 kg

ACETAMINOPHEN, USP